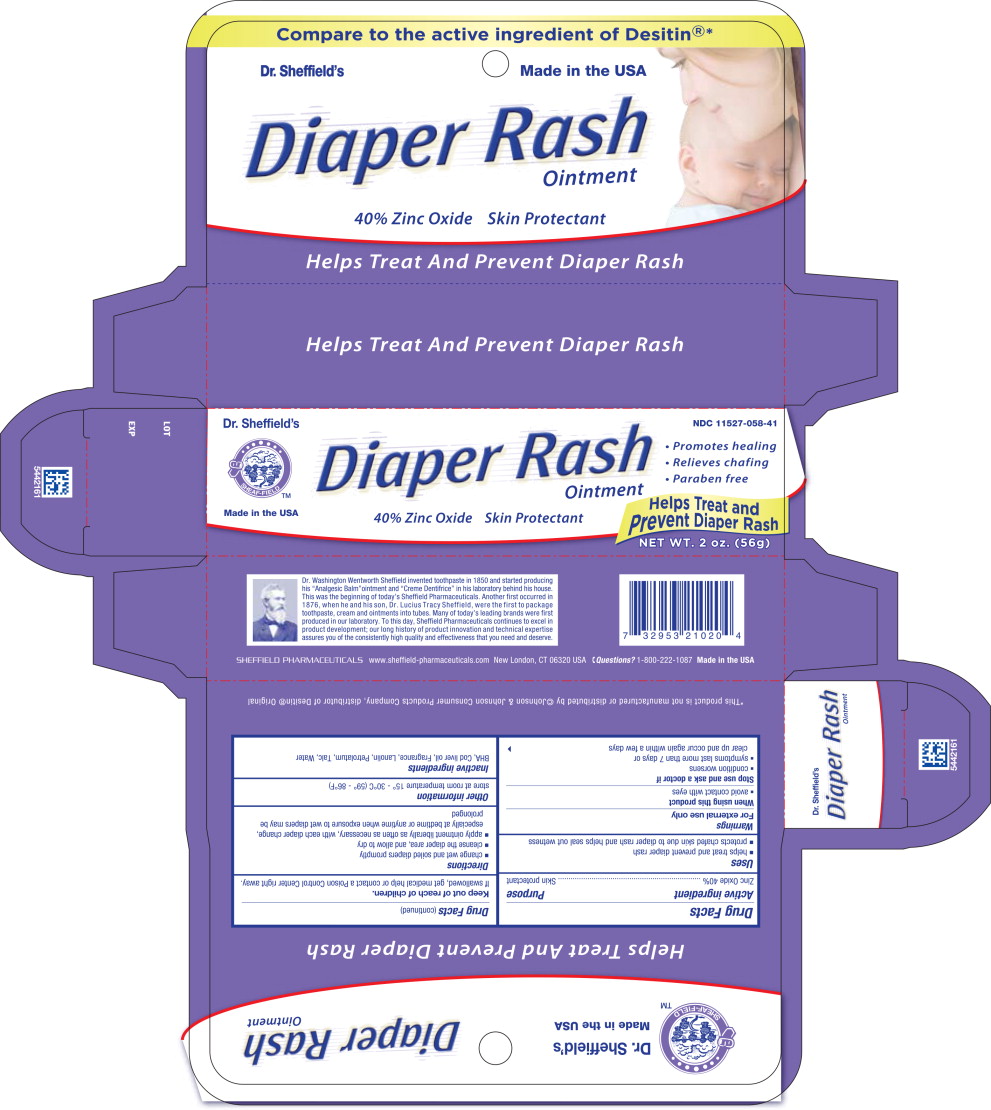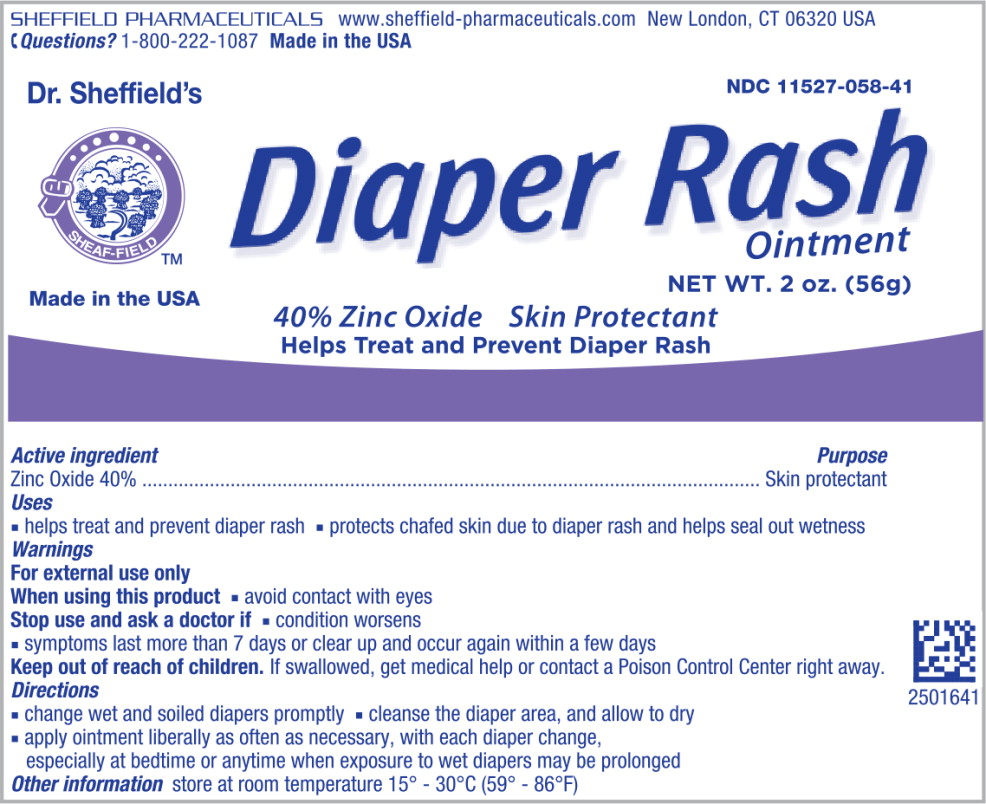 DRUG LABEL: Dr. Sheffield Diaper Rash
NDC: 11527-058 | Form: OINTMENT
Manufacturer: Sheffield Pharmaceuticals LLC
Category: otc | Type: HUMAN OTC DRUG LABEL
Date: 20231128

ACTIVE INGREDIENTS: ZINC OXIDE 400 mg/1 g
INACTIVE INGREDIENTS: BUTYLATED HYDROXYANISOLE; COD LIVER OIL; LANOLIN; PETROLATUM; TALC; WATER

Drug Facts

Active ingredient

Zinc Oxide 40%

Purpose

Skin protectant

Uses

- helps treat and prevent diaper rash
- protects chafed skin due to diaper rash and helps seal out wetness

Warnings

When using this product

- avoid contact with eyes

Stop use and ask a doctor if

- condition worsens
- symptoms last more than 7 days or clear up and occur again within a few days

Keep out of reach of children.

If swallowed, get medical help or contact a Poison Control Center right away.

Directions

- change wet and soiled diapers promptly
- cleanse the diaper area, and allow to dry
- apply ointment liberally as often as necessary, with each diaper change, especially at bedtime or anytime when exposure to wet diapers may be prolonged

Other information

store at room temperature 15° - 30°C (59° - 86°F)

Inactive ingredients

BHA, Cod liver oil, Fragrance, Lanolin, Petrolatum, Talc, Water

Principal Display Panel - Carton Label

NDC 11527-058-41

Dr. Sheffield's

Made in the USA

Diaper Rash
Ointment

40% Zinc Oxide Skin Protectant

• Promotes healing

• Relieves chafing

• Paraben free

Helps Treat and
Prevent Diaper Rash

NET WT. 2 oz. (56g)

Principal Display Panel - Tube Label

NDC 11527-058-41

Dr. Sheffield's

Made in the USA

Diaper Rash
Ointment

NET WT. 2 oz. (56g)

40% Zinc Oxide Skin Protectant

Helps Treat and Prevent Diaper Rash